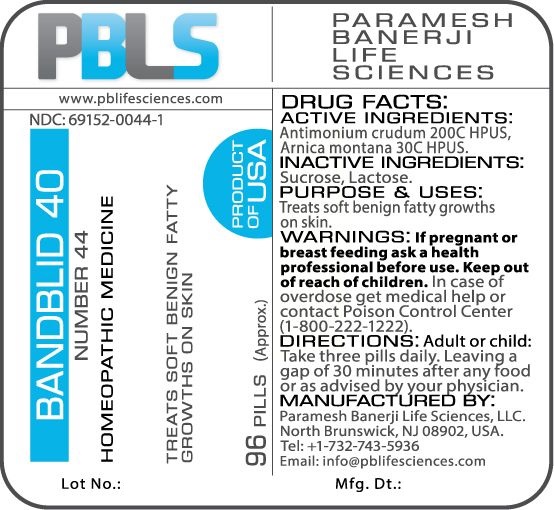 DRUG LABEL: Bandblid 40 (Number 44)
NDC: 69152-0044 | Form: PELLET
Manufacturer: Paramesh Banerji Life Sciences LLC
Category: homeopathic | Type: HUMAN OTC DRUG LABEL
Date: 20170322

ACTIVE INGREDIENTS: ARNICA MONTANA 30 [hp_C]/1 1; ANTIMONY TRISULFIDE 200 [hp_C]/1 1
INACTIVE INGREDIENTS: SUCROSE; LACTOSE

DRUG FACTS: Active Ingredients

Antimonium crudum 200C HPUS, Arnica montana 30C HPUS

Inactive Ingredients

Sucrose, Lactose

Purpose

Treats soft benign fatty growths on skin

Uses

Treats soft benign fatty growths on skin

Warnings

If pregnant or breast feeding ask a health professional before use.

Keep out of reach of children. In case of overdose, get medical help or contact a Poison Control Center (1-800-222-1222) right away.

Direction

Adult or child: Take three pills daily. Leaving a gap of 30 minutes after any food or as advised by your physician.

Manufactured by

Paramesh Banerji Life Sciences, LLC.

North Brunswick, NJ 08902, USA.

Tel: +1-732-743-5936

Email: info@pblifesciences.com

Principal Display Panel

NDC: 69152-0044-1

Bandblid 40

Number 44

Homeopathic Medicine

Treats soft benign fatty growth on skin

96 Pills (Approx.)

Product of USA